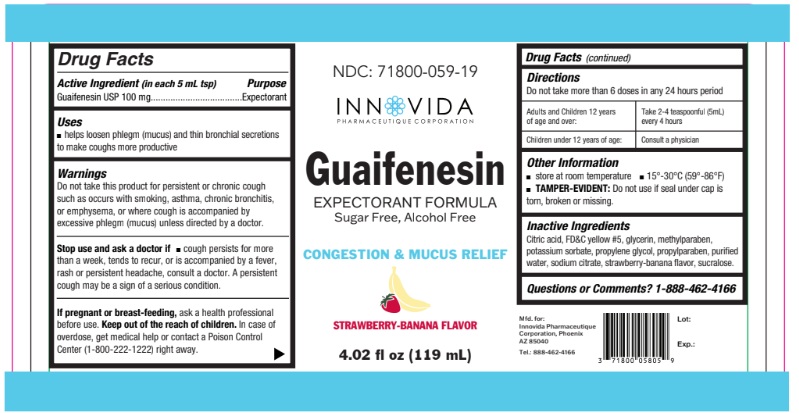 DRUG LABEL: Guaifenesin STRAWBERRY-BANANA FLAVOR
NDC: 71800-059 | Form: LIQUID
Manufacturer: Innovida Pharmaeutique Corporation
Category: otc | Type: HUMAN OTC DRUG LABEL
Date: 20250618

ACTIVE INGREDIENTS: GUAIFENESIN 100 mg/5 mL
INACTIVE INGREDIENTS: CITRIC ACID; FD&C RED NO. 40; GLYCERIN; MENTHOL; METHYLPARABEN; POTASSIUM SORBATE; PROPYLENE GLYCOL; PROPYLPARABEN; WATER; SODIUM CITRATE; SUCRALOSE; STRAWBERRY

Active Ingredient

Guaifenesin,USP 100 mg (in each 5ml tsp)

Purpose

Expectorant

Uses

- helps loosen phlegm (mucus) and thin bronchial secretions to make coughs more productive

Warnings

Do not take this product for persistent or chronic cough such as occurs with smoking, asthma, chronic bronchitis, or emphysema, or where cough is accompanied by excessive phlegm (mucus) unless directed by a doctor.

Stop use and ask a doctor if■ cough persists for more than a week, tends to recur, or is accompanied by a fever, rash or persistent headache, consult a doctor. A persistent cough may be a sign of a serious condition.

If pregnant or breast-feeding, ask a health professional before use. Keep out of the reach of children. In case of overdose, get medical help or contact a Poison Control Center (1-800-222-1222) right away.

Directions

- Do not take more than 6 doses in any 24 hours period

age | dose
Adults and Children 12 years of age and over:; Children under 12 years of age: | Take 2-4 teaspoonful (5mL) every 4 hours; Consult a physician

Other Information

- store at room temperature ■ 15°-30°C (59°-86°F)
- TAMPER-EVIDENT: Do not use if seal under cap is torn, broken or missing.

Inactive Ingredients

Citric acid, FD&C yellow #5, glycerin, methylparaben, potassium sorbate, propylene glycol, propylparaben, purified water, sodium citrate, strawberry-banana flavor, sucralose.